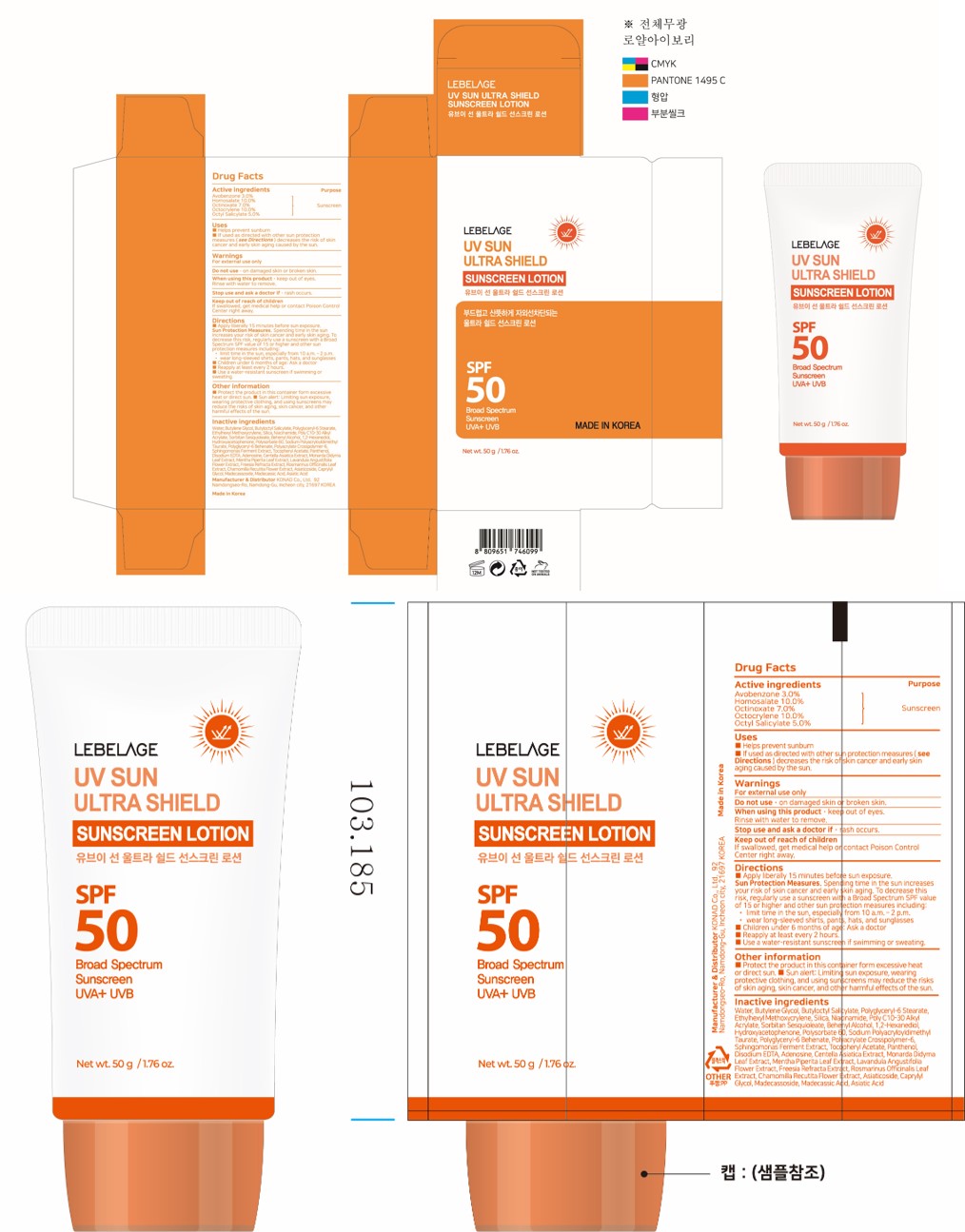 DRUG LABEL: LEBELAGE UV SUN ULTRA SHIELD SUN SCREENLOTION 50g
NDC: 85948-251 | Form: LOTION
Manufacturer: DONGDONGGURIMOO CO.,LTD.
Category: otc | Type: HUMAN OTC DRUG LABEL
Date: 20260122

ACTIVE INGREDIENTS: AVOBENZONE 1.5 g/50 g; OCTINOXATE 3.5 g/50 g; OCTOCRYLENE 5 g/50 g; HOMOSALATE 5 g/50 g; OCTISALATE 2.5 g/50 g
INACTIVE INGREDIENTS: POLYGLYCERYL-6 BEHENATE; AMMONIUM ACRYLOYLDIMETHYLTAURATE, DIMETHYLACRYLAMIDE, LAURYL METHACRYLATE AND LAURETH-4 METHACRYLATE COPOLYMER, TRIMETHYLOLPROPANE TRIACRYLATE CROSSLINKED (45000 MPA.S); .ALPHA.-TOCOPHEROL ACETATE; ADENOSINE; CENTELLA ASIATICA TRITERPENOIDS; MONARDA DIDYMA LEAF; ROSEMARY; ASIATICOSIDE; MADECASSIC ACID; ETHYLHEXYL METHOXYCRYLENE; NIACINAMIDE; DOCOSANOL; POLYSORBATE 60; POLYGLYCERYL-6 STEARATE; SODIUM POLYACRYLOYLDIMETHYL TAURATE; BUTYLOCTYL SALICYLATE; BUTYLENE GLYCOL; 1,2-HEXANEDIOL; PANTHENOL; WATER; SILICON DIOXIDE; SORBITAN SESQUIOLEATE; HYDROXYACETOPHENONE; MADECASSOSIDE

Active ingredients

avobenzone 3.0%

Homosalate 10.0%

Octinoxate 7.0%

Octocrylene 10.0%

Octisalate 5.0%

Purpose

SUNSCREEN

Uses

helps prevent sunburn • if used as directed with other sun

protection measures (see Directions) decreases the risk of skin

cancer and early skin aging caused by the sun

Warnings

For external use only

Do not use

• on damaged skin or broken skin

When using this product

• keep out of eyes. Rinse with water to remove.

Stop use

and ask a doctor if • rash occurs

Keep out of reach

of children If swallowed, get medical help or contact a Poison Control Center right away.

Directions

■ apply liberally 15 minutes before sun exposure.

Sun Protection Measures. Spending time in the sun increases your risk of skin cancer and early skin aging. To decrease this risk, regularly use a sunscreen with a Broad Spectrum SPF value of 15 or higher and other sun protection measures including:

• limit time in the sun, especially from 10 a.m. - 2 p.m.

• wear long-sleeved shirts, pants, hats, and sunglasses

■ children under 6 months of age: Ask a doctor

■ reapply at least every 2 hours

■ use a water-resistant sunscreen if swimming or sweating

Other information

■ protect the product from excessive heat and direct sun ■ Sun alert: Limiting sun exposure, wearing protective clothing, and using sunscreens may reduce the risks of skin aging, skin cancer, and other harmful effects of the sun.

Inactive ingredients

Water, Butyloctyl Salicylate, Butylene Glycol, Polyglyceryl-6 Stearate, Ethylhexyl Methoxycrylene, Silica, Niacinamide, Poly C10-30 Alkyl Acrylate, Sorbitan Sesquioleate, Behenyl Alcohol, 1,2-Hexanediol, Hydroxyacetophenone, Polysorbate 60, Sodium Polyacryloyldimethyl Taurate, Polyglyceryl-6 Behenate, Tocopheryl Acetate, Panthenol, Polyacrylate Crosspolymer-6, Sphingomonas Ferment Extract, Disodium EDTA, Adenosine, Centella Asiatica Extract, Monarda Didyma Leaf Extract, Mentha Piperita Leaf Extract, Lavandula Angustifolia Flower Extract, Freesia Refracta Extract, Rosmarinus Officinalis Leaf Extract, Chamomilla Recutita Flower Extract, Asiaticoside, Madecassoside, Madecassic Acid, Asiatic Acid